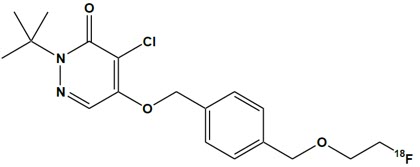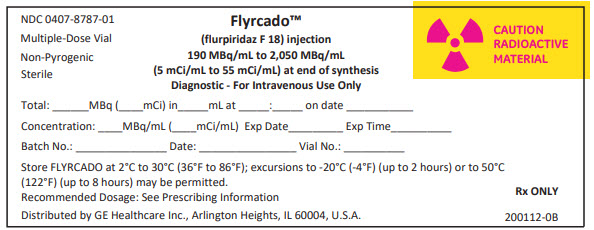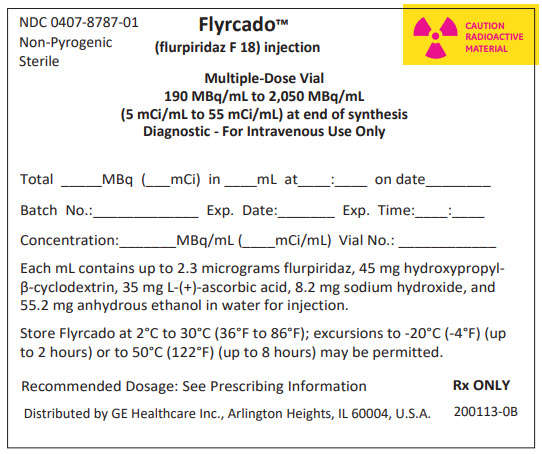 DRUG LABEL: Flyrcado
NDC: 0407-8787 | Form: INJECTION
Manufacturer: GE Healthcare Inc.
Category: prescription | Type: HUMAN PRESCRIPTION DRUG LABEL
Date: 20251230

ACTIVE INGREDIENTS: FLURPIRIDAZ F-18 55 mCi/1 mL
INACTIVE INGREDIENTS: ALCOHOL; ASCORBIC ACID; HYDROXYPROPYL BETADEX; SODIUM HYDROXIDE; WATER

HIGHLIGHTS OF PRESCRIBING INFORMATION

These highlights do not include all the information needed to use FLYRCADO™ safely and effectively. See full prescribing information for FLYRCADO.
FLYRCADO™ (flurpiridaz F 18) injection, for intravenous use
Initial U.S. Approval: 2024

1 INDICATIONS AND USAGE

FLYRCADO is a radioactive diagnostic drug indicated for positron emission tomography (PET) myocardial perfusion imaging (MPI) under rest or stress (pharmacologic or exercise) in adult patients with known or suspected coronary artery disease (CAD) to evaluate for myocardial ischemia and infarction. (1)

2 DOSAGE AND ADMINISTRATION

- Administer FLYRCADO via intravenous injection. (2.2)
- When rest and stress imaging are conducted on the same day, the recommended administered activities are (2.2):
  - Rest imaging: 93 MBq to 111 MBq (2.5 mCi to 3 mCi)
  - Pharmacologic stress imaging: 222 MBq to 241 MBq (6 mCi to 6.5 mCi)
  - Exercise stress imaging: 333 MBq to 352 MBq (9 mCi to 9.5 mCi)
- When rest and stress imaging are conducted over two days, the recommended rest and stress administered activities, for both pharmacologic and exercise stress, are 93 MBq to 111 MBq (2.5 mCi to 3 mCi). (2.2)
- See full prescribing information for radiation safety, preparation, administration, imaging, and radiation dosimetry information. (2.1, 2.2, 2.3, 2.4)

3 DOSAGE FORMS AND STRENGTHS

Injection: 190 MBq/mL to 2,050 MBq/mL (5 mCi/mL to 55 mCi/mL) of flurpiridaz F 18 at end of synthesis in a shielded multiple-dose vial with up to 30 mL fill volume (3)

4 CONTRAINDICATIONS

None (4)

5 WARNINGS AND PRECAUTIONS

- Risk associated with exercise or pharmacologic stress: Serious adverse reactions such as myocardial infarction, arrhythmia, hypotension, broncho-constriction, stroke, and seizures may occur. Perform stress testing in the setting where cardiac resuscitation equipment and trained staff are readily available. When pharmacologic stress is selected, perform the procedure in accordance with the pharmacologic stress agent's prescribing information. (5.1)
- Radiation risks: Ensure safe handling to minimize radiation exposure to patients and health care providers. (5.2)

6 ADVERSE REACTIONS

Most common adverse reactions occurring during FLYRCADO PET MPI under rest and stress (pharmacologic or exercise) (incidence ≥ 2%) are dyspnea, headache, angina pectoris, chest pain, fatigue, ST segment changes, flushing, nausea, abdominal pain, dizziness, and arrhythmia. (6.1)

To report SUSPECTED ADVERSE REACTIONS, contact GE HealthCare at 1-800-654-0118 or FDA at 1-800-FDA-1088 or www.fda.gov/medwatch.

8 USE IN SPECIFIC POPULATIONS

Lactation: Temporarily discontinue breastfeeding. A lactating woman should pump and discard breastmilk for at least 8 hours after FLYRCADO administration. (8.2)

FULL PRESCRIBING INFORMATION

1 INDICATIONS AND USAGE

FLYRCADO is indicated for positron emission tomography (PET) myocardial perfusion imaging (MPI) under rest or stress (pharmacologic or exercise) in adult patients with known or suspected coronary artery disease (CAD) to evaluate for myocardial ischemia and infarction.

2 DOSAGE AND ADMINISTRATION

2.1 Radiation Safety – Drug Handling

Handle FLYRCADO with appropriate safety measures to minimize radiation exposure [see Warnings and Precautions (5.2)]. Use waterproof gloves and effective shielding, including lead-glass syringe shields, when handling and administering FLYRCADO.

Radioactive drugs should be used by or under the control of healthcare providers who are qualified by specific training and experience in the safe use and handling of radionuclides, and whose experience and training have been approved by the appropriate governmental agency authorized to license the use of radionuclides.

2.2 Recommended Dosage, Preparation, and Administration Instructions

Recommended Dosage

- The recommended activity for each type of examination is presented in Table 1.
- Administer two doses by intravenous injection, one for rest imaging and one for stress imaging, using either pharmacologic or exercise stress, in either a 1-day or 2-day protocol.
- If performing a combined exercise/pharmacologic stress protocol, administer the recommended activity for pharmacologic stress.
- When rest and stress imaging are performed on the same day, the recommended minimum stress activity is 2-fold the rest activity for pharmacologic stress and 3-fold the rest activity for exercise stress to provide adequate image quality and obscure residual signal from the first acquisition.
- The recommended maximum total volume administered in one day is 6.1 mL.

Table 1 – Recommended Administered Activities of FLYRCADO in Adults for Rest and Stress Imaging Using Pharmacologic or Exercise Stress in a 1-Day or 2-Day Protocol
Length of Protocol | Activity for Rest Imaging | Activity for Stress Imaging
Length of Protocol | Activity for Rest Imaging | Pharmacologic | Exercise
1 day | 93 MBq to 111 MBq (2.5 mCi to 3 mCi) | 222 MBq to 241 MBq (6 mCi to 6.5 mCi) | 333 MBq to 352 MBq (9 mCi to 9.5 mCi)
2 days | 93 MBq to 111 MBq (2.5 mCi to 3 mCi) | 93 MBq to 111 MBq (2.5 mCi to 3 mCi) | 93 MBq to 111 MBq (2.5 mCi to 3 mCi)

Patient Preparation

Instruct patients to drink water to ensure adequate hydration prior to administration of FLYRCADO and to continue drinking and voiding frequently during the first hours following administration to reduce radiation exposure [see Warnings and Precautions (5.2)].

Drug Preparation

- Use aseptic technique and radiation shielding to withdraw and administer FLYRCADO.
- Calculate the necessary volume to administer based on calibration time and activity using a suitably calibrated instrument.
- Visually inspect FLYRCADO for particulate matter and discoloration prior to administration and do not use if either is observed.
- Ensure the correct syringe is used and has adequate volume (at least 1 mL to 2 mL) so that the activity in the syringe can be administered without excessive dead volume loss.
- Measure patient dose using a dose calibrator immediately before administration.
- Do not use and discard FLYRCADO 8 hours after end of synthesis or when the activity falls below the activity requirement at the time of injection, whichever is earlier.
- FLYRCADO may be diluted aseptically with 0.9% Sodium Chloride Injection, USP. Diluted product should be used within 8 hours after end of synthesis or when the activity falls below the activity requirement at the time of injection, whichever is earlier.
- Dispose of unused product in a safe manner and in compliance with applicable regulations.

Administration Instructions

- Administer FLYRCADO via intravenous injection as a bolus lasting less than 10 seconds and immediately follow with a flush of 0.9% Sodium Chloride Injection, USP.
- The minimum time between rest and stress dose administration is:
  - 30 minutes when using pharmacologic stress
  - 60 minutes when using exercise stress
- When using pharmacologic stress, administer FLYRCADO at the time of peak vasodilation according to the prescribing information for the stress agent, using an intravenous port different from the one used for the stress agent.
- When using exercise stress, administer FLYRCADO after the patient reaches at least 85% of their age-predicted maximum heart rate or exhibits ischemic signs or symptoms. The patient should then continue to exercise for approximately 1 minute to 2 minutes after the injection. If the patient cannot achieve the target heart rate, the examination may be converted to pharmacologic stress.

2.3 Image Acquisition Instructions

For rest and stress imaging, image reconstruction should include attenuation correction.

Rest Imaging

Begin the PET acquisition 5 minutes after FLYRCADO administration and acquire images for 10 minutes using a scanner in 3D mode.

Pharmacologic Stress Imaging

Begin the PET acquisition 5 minutes after FLYRCADO administration and acquire images for 10 minutes using a scanner in 3D mode.

Optionally, dynamic imaging may be performed, starting immediately prior to the injection of FLYRCADO.

Exercise Stress Imaging

Once the patient has been positioned on the scanner and respiration has begun to return to normal, begin image acquisition (about 15 minutes to 25 minutes after administration of FLYRCADO). Acquire images for 10 minutes using a scanner in 3D mode.

2.4 Radiation Dosimetry

Table 2 shows the estimated radiation absorbed doses per unit of injected activity.

Table 2 – Estimated Radiation Absorbed Doses in Organs/Tissues from Intravenous Administration of FLYRCADO in Adults
Organ | Absorbed Dose per Unit of Administered Activity (mGy/MBq)
Organ | Rest | Pharmacologic Stress [The pharmacologic stress agent used was adenosine.] | Exercise Stress
Adrenals | 0.016 | 0.016 | 0.014
Bone surfaces | 0.019 | 0.019 | 0.02
Brain | 0.025 | 0.022 | 0.011
Breasts | 0.009 | 0.009 | 0.01
Gallbladder Wall | 0.017 | 0.018 | 0.015
Gastrointestinal Tract
Stomach Wall | 0.04 | 0.033 | 0.024
Small Intestine Wall | 0.013 | 0.012 | 0.014
Upper Large Intestine Wall | 0.013 | 0.012 | 0.014
Lower Large Intestine Wall | 0.012 | 0.011 | 0.014
Heart Wall | 0.048 | 0.09 | 0.039
Kidneys | 0.066 | 0.057 | 0.027
Liver | 0.039 | 0.044 | 0.015
Lungs | 0.011 | 0.012 | 0.012
Muscle | 0.01 | 0.01 | 0.012
Ovaries | 0.012 | 0.012 | 0.014
Pancreas | 0.016 | 0.016 | 0.015
Red Marrow | 0.016 | 0.018 | 0.015
Salivary Glands | 0.035 | 0.076 | 0.007
Skin | 0.008 | 0.008 | 0.009
Spleen | 0.016 | 0.012 | 0.013
Testes | 0.009 | 0.009 | 0.011
Thymus | 0.011 | 0.012 | 0.013
Thyroid | 0.032 | 0.036 | 0.014
Urinary Bladder Wall | 0.023 | 0.021 | 0.016
Uterus | 0.012 | 0.012 | 0.014
Total Body | 0.012 | 0.012 | 0.012
Effective Dose (mSv/MBq) | 0.019 | 0.019 | 0.015

The whole-body effective dose resulting from the administration of maximal activity of FLYRCADO of 111 MBq at rest, 241 MBq during pharmacological stress, and 352 MBq during exercise stress is, respectively, 2.1 mSv, 4.6 mSv, and 5.3 mSv. Under the same conditions, the absorbed dose to the target organ (heart wall) is 5.3 mGy, 22 mGy, and 14 mGy for each administered activity, respectively.

The use of a CT scan to calculate attenuation correction for the reconstruction of FLYRCADO PET images (as done in PET/CT imaging) will add radiation exposure.

3 DOSAGE FORMS AND STRENGTHS

Injection: 190 MBq/mL to 2,050 MBq/mL (5 mCi/mL to 55 mCi/mL) of flurpiridaz F 18 at end of synthesis as a clear, colorless to yellow solution in a shielded multiple-dose vial with up to 30 mL fill volume.

4 CONTRAINDICATIONS

None.

5 WARNINGS AND PRECAUTIONS

5.1 Risks Associated with Exercise or Pharmacologic Stress

Patients evaluated with exercise or pharmacologic stress may experience serious adverse reactions such as myocardial infarction, arrhythmia, hypotension, bronchoconstriction, stroke, and seizure. Perform stress testing in the setting where cardiac resuscitation equipment and trained staff are readily available. When pharmacologic stress is selected as an alternative to exercise, perform the procedure in accordance with the pharmacologic stress agent's prescribing information.

5.2 Radiation Risks

FLYRCADO contributes to a patient's overall long-term cumulative radiation exposure. Long-term cumulative radiation exposure is associated with an increased risk of cancer. Ensure safe handling to minimize radiation exposure to patients and health care providers [see Dosage and Administration (2.1, 2.4)]. Advise patients to hydrate before and after administration and to void frequently after administration.

6 ADVERSE REACTIONS

The following serious adverse reactions are described elsewhere in the labeling:

- Risks Associated with Exercise or Pharmacologic Stress [see Warnings and Precautions (5.1)]

6.1 Clinical Trials Experience

Because clinical trials are conducted under widely varying conditions, adverse reaction rates observed in the clinical trials of a drug cannot be directly compared to rates in the clinical trials of another drug and may not reflect the rates observed in clinical practice.

The safety of FLYRCADO was evaluated in 1,600 subjects in clinical studies, including 1,575 (98%) subjects with known or suspected coronary artery disease and 25 (2%) healthy subjects. All 1,600 subjects were dosed under rest conditions, with a mean dose of 102 MBq (2.8 mCi) FLYRCADO. A total of 1,568 (98%) subjects were also dosed under stress (exercise or pharmacologic) conditions, with a mean activity of 252 MBq (6.8 mCi) FLYRCADO by intravenous route. The demographic characteristics of the study population were 31% female, mean age 62 years (range 19 years to 90 years), 81% White, 11% Black or African American, 1% Asian, and 7% other or unreported race, and 10% Hispanic or Latino, 81% Not Hispanic or Latino, and 9% unreported ethnicity.

Stress testing procedures are associated with serious adverse reactions [see Warnings and Precautions (5.1)]. Adverse reactions occurring in ≥2% subjects receiving FLYRCADO during PET MPI under rest and stress (pharmacologic or exercise) are presented in Table 3.

Table 3. Adverse Reactions Reported in ≥2% of Subjects During FLYRCADO PET MPI Under Rest and Stress (Pharmacologic or Exercise)
Adverse Reaction | FLYRCADO PET MPI Under Rest and Stress (Pharmacologic or Exercise) N=1,600 [Includes 32 subjects who received only one dose at rest.] %
Dyspnea | 17
Headache | 15
Angina pectoris | 10
Chest pain | 8
Fatigue | 7
ST segment changes | 6
Flushing | 5
Nausea | 4
Abdominal pain | 4
Dizziness | 4
Arrhythmia | 4

Adverse reactions occurring during FLYRCADO PET MPI under rest and stress (pharmacologic or exercise) in <2% of subjects included diarrhea, palpitations, back pain, cardiac conduction disturbance, rash, dysgeusia, cough, hypotension, anxiety, vomiting, pruritus, bronchospasm, dry mouth, blood pressure elevation, syncope, and wheezing.

8 USE IN SPECIFIC POPULATIONS

8.1 Pregnancy

Risk Summary

There are no data on use of flurpiridaz F 18 in pregnant women to evaluate for a drug-associated risk of major birth defects, miscarriage, or other adverse maternal or fetal outcomes.

All radiopharmaceuticals, including FLYRCADO, have the potential to cause fetal harm depending on the fetal stage of development and the magnitude of the radiation dose. If considering FLYRCADO administration to a pregnant woman, inform the patient about the potential for adverse pregnancy outcomes based on the radiation dose from flurpiridaz F 18 and the gestational timing of exposure.

FLYRCADO contains ethanol (a maximum daily dose of 337 mg anhydrous ethanol). The lower limit of safety for ethanol use during pregnancy has not been established. Published studies have demonstrated that ethanol is associated with fetal harm including central nervous system abnormalities, behavioral disorders, and impaired intellectual development. If considering FLYRCADO administration to a pregnant woman, inform the patient about the potential for adverse pregnancy outcomes associated with ethanol exposure during pregnancy.

The background risk of major birth defects and miscarriage for the indicated population is unknown. All pregnancies have a background risk of birth defect, loss, or other adverse outcomes. In the U.S. general population, the estimated background risk of major birth defects and miscarriage in clinically recognized pregnancies is 2% to 4% and 15% to 20%, respectively.

8.2 Lactation

Risk Summary

There are no data on the presence of flurpiridaz F 18 or its metabolites in human milk or animal milk, the effects on the breastfed infant, or the effects on milk production. Based on clinical guidelines, exposure of FLYRCADO to a breastfed infant can be minimized by advising a lactating woman to temporarily discontinue breastfeeding and to pump and discard breast milk for a minimum of 8 hours after administration of FLYRCADO. The developmental and health benefits of breastfeeding should be considered along with the mother's clinical need for FLYRCADO and any potential adverse effects on the breastfed child from FLYRCADO or from the underlying maternal condition.

8.4 Pediatric Use

Safety and effectiveness of FLYRCADO in pediatric patients have not been established.

8.5 Geriatric Use

Of 1,600 subjects in clinical studies of FLYRCADO, 720 (45%) were 65 years of age and over and 181 (11%) were 75 years of age or older. No overall differences in safety or effectiveness of FLYRCADO have been observed between patients 65 years of age and older and younger adult patients.

11 DESCRIPTION

11.1 Chemical Characteristics

FLYRCADO (flurpiridaz F 18) injection is a radioactive diagnostic drug for intravenous use. The molecular formula of flurpiridaz F 18 is C18H22Cl^18FN2O3, the molecular mass is 367.8, and the structural formula is:

Chemically, flurpiridaz F 18 is 2-tert-butyl-4-chloro-5-[[4-(2-(^18F)fluoranylethoxymethyl)phenyl]methoxy]pyridazin-3-one.

FLYRCADO is a sterile, preservative-free, non-pyrogenic, clear, colorless to yellow radioactive solution. Each mL contains 190 MBq to 2,050 MBq (5 mCi to 55 mCi) of flurpiridaz F 18 at end of synthesis, up to 2.3 mcg flurpiridaz, and the following inactive ingredients: 45 mg hydroxypropyl-β-cyclodextrin (as a solubilizer and co-radiostabilizer), 35 mg L-(+)-ascorbic acid (as a radiostabilizer), 8.2 mg sodium hydroxide, and 55.2 mg anhydrous ethanol, in water for injection. The pH of the solution is between 5.5 and 8.

11.2 Physical Characteristics

Fluorine-18 decays by positron (β+) emission and has a half-life of 109.8 minutes. The principal photons useful for diagnostic imaging are the 511 keV gamma photons, resulting from the interaction of the emitted positron with an electron. Principal emission data for fluorine-18 are shown in Table 4.

Table 4 – Principal Radiation Emission Data for Fluorine-18
Radiation/Emission | % per Disintegration | Mean Energy (keV)
Positron | 96.7 | 249.8
Gamma | 193.5 | 511

11.3 External Radiation

The point source air-kerma rate constant for fluorine-18 is 3.74E-17 Gy m^2/(Bq s); this coefficient was formerly defined as the specific gamma-ray constant of 5.7 R/hr/mCi at 1 cm. The first half-value thickness of lead (Pb) for fluorine-18 gamma rays is approximately 6 mm. The relative reduction of radiation emitted by fluorine-18 that results from various thicknesses of lead shielding is shown in Table 5. The use of about 8 cm of Pb will decrease the radiation transmission (i.e., exposure) by a factor of about 10,000.

Table 5 - Radiation Attenuation of 511 keV Gamma Rays by Lead Shielding
Shielding Thickness cm of Lead (Pb) | Coefficient of Attenuation
0.6 | 0.5
2 | 0.1
4 | 0.01
6 | 0.001
8 | 0.0001

12 CLINICAL PHARMACOLOGY

12.1 Mechanism of Action

Flurpiridaz F 18 is an analog of the mitochondrial complex 1 (MC-1) inhibitor, pyridaben. Flurpiridaz F 18 is extracted by the myocardium proportional to the blood flow and binds to heart tissue that has biologically active mitochondria. Therefore, radioactivity in viable myocardium is higher than in infarcted tissue.

12.2 Pharmacodynamics

The relationship between flurpiridaz F 18 plasma concentrations and successful imaging was not explored in clinical trials.

12.3 Pharmacokinetics

The pharmacokinetics of flurpiridaz F 18 were evaluated in healthy subjects. Blood radioactivity peaked at 2.3 minutes with blood clearance followed by a rise and plateau at around 3% of the 296 MBq (8 mCi) flurpiridaz F 18 intravenous dose until 7 hours post administration. The fluorine-18 radioactivity in blood during the first 15-minutes post administration was associated with flurpiridaz while it was associated with flurpiridaz metabolites thereafter.

Distribution

Flurpiridaz F 18 distributes to the liver (19% of injected activity), kidneys (9%), brain (8%), and heart wall (3%) about 10 minutes post-dose. The heart wall radioactivity was retained for 1 hour after administration.

Elimination

Flurpiridaz F 18 and its metabolites were cleared from blood within 48 hours.

Metabolism

Flurpiridaz F 18 was shown to undergo biotransformation to numerous polar metabolites.

Excretion

Following intravenous administration of a single dose of ^3H-radiolabeled flurpiridaz, 63% of the administered dose was recovered in urine (0% unchanged flurpiridaz) and 30% in feces (0% unchanged flurpiridaz).

Specific Populations

No clinically significant differences in the pharmacokinetics of flurpiridaz F 18 were observed for age, sex, body mass index, diabetic status, mild hepatic impairment (Child Pugh A), or renal impairment (eGFR ≥19 to 89 mL/min). The effect of moderate to severe hepatic impairment (Child Pugh B and C) or end stage renal disease on flurpiridaz F 18 pharmacokinetics has not been evaluated.

13 NONCLINICAL TOXICOLOGY

13.1 Carcinogenesis, Mutagenesis, Impairment of Fertility

Carcinogenesis

No carcinogenicity studies of flurpiridaz have been conducted.

Mutagenesis

Flurpiridaz did not demonstrate mutagenic potential in an in vitro bacterial reverse mutation assay (Ames test), in an in vitro chromosome aberration assay in Chinese hamster ovary cells, or in an in vivo rat micronucleus assay.

14 CLINICAL STUDIES

14.1 Overview of Clinical Studies

The safety and effectiveness of FLYRCADO were evaluated in two prospective, multicenter, open-label clinical studies in adults with either suspected coronary artery disease (CAD) (Study 1: NCT03354273) or known or suspected CAD (Study 2: NCT01347710).

Subjects received two injections of FLYRCADO: one at rest and one during stress [see Dosage and Administration (2.2, 2.3)]. For the FLYRCADO stress injection, subjects received either a pharmacologic stress agent or engaged in exercise stress. PET myocardial perfusion imaging (MPI) was performed at both rest and stress using cardiac gating and low-dose CT attenuation correction. Subjects also received rest and stress SPECT MPI using technetium Tc 99m sestamibi or technetium Tc 99m tetrofosmin on a different day from the PET MPI. The stress modality was to be the same for PET and SPECT.

Stress and rest images were displayed side-by-side for the assessment of perfusion and wall motion abnormalities. Three qualified readers, blinded to clinical data, performed independent assessment of each subject's rest and stress images, with each recording an overall qualitative diagnosis of normal, ischemia, ischemia plus scar, or scar. For analyses of sensitivity and specificity, normal was considered image negative and all other diagnoses were considered image positive.

14.2 Suspected Coronary Artery Disease

Study 1 evaluated the sensitivity and specificity of FLYRCADO PET MPI for the detection of significant CAD in subjects with suspected CAD who were scheduled for invasive coronary angiography (ICA).

A total of 578 subjects were evaluable for effectiveness, having rest and stress imaging and evaluable truth standard data. Subjects ranged in age from 26 years to 88 years, with a mean age of 64 years. A total of 188 (33%) were female, and 473 (82%) were White, 35 (6%) were Black or African American, 6 (1%) were Asian, and 64 (11%) were other races or not reported. In addition, 79 subjects (14%) reported Hispanic/Latino ethnicity. Pharmacologic stress was performed in 83% of subjects and exercise stress in 17% of subjects.

The sensitivity and specificity of FLYRCADO PET MPI for detection of significant CAD, defined as the presence of significant stenosis in at least one major epicardial coronary artery or major branch by quantitative coronary angiography (QCA) are reported in Table 6. Results for both ≥50% stenosis and a secondary analysis using ≥70% stenosis as the threshold for significant CAD are shown.

Table 6. Diagnostic Performance of FLYRCADO PET MPI in Study 1 (N = 578 [Includes 12 subjects who had reference standard images categorized as uninterpretable by the central reader but were forced to be diagnosed as positive or negative (2 subjects as positive and 10 subjects as negative).])
 | ≥50% Stenosis Reference Standard |  | ≥70% Stenosis Reference Standard
Reader | Sensitivity (95% CI) N=249 | Specificity (95% CI) N=329 | Sensitivity (95% CI) N=127 | Specificity (95% CI) N=449
Reader 1 | 77% (72%, 82%) | 66% (61%, 71%) | 91% (86%, 96%) | 58% (54%, 63%)
Reader 2 | 74% (68%, 79%) | 70% (65%, 75%) | 87% (82%, 93%) | 62% (58%, 67%)
Reader 3 | 89% (85%, 93%) | 53% (47%, 58%) | 97% (94%, 100%) | 44% (39%, 49%)
Abbreviations: CI = confidence interval, MPI = myocardial perfusion imaging

From a blinded re-evaluation of 60 randomly selected PET MPI images presented during the main reading sessions, intra-reader kappa ranged from 0.71 to 0.93 for the three readers.

Using a 50% stenosis threshold, sensitivity of SPECT MPI was 61% to 76% for the three readers, with the lower bound of the 95% confidence intervals ranging from 55% to 70%, and specificity of SPECT MPI was 51% to 65%, with the lower bound of the 95% confidence intervals ranging from 46% to 60%.

14.3 Known or Suspected Coronary Artery Disease

Study 2 evaluated the sensitivity and specificity of FLYRCADO PET MPI for the detection of significant CAD in subjects with known or suspected CAD who had ICA without intervention within 60 days prior to imaging or were scheduled for ICA.

A total of 755 subjects were evaluable for effectiveness, having rest and stress imaging for FLYRCADO PET and evaluable truth standard data. Subjects ranged in age from 36 years to 90 years, with a mean age of 63 years. A total of 235 (31%) were female, and 619 (82%) were White, 101 (13%) were Black or African American, 8 (1%) were Asian, and 24 (4%) were other races or not reported. Pharmacologic stress was performed in 71% of subjects and exercise stress in 29% of subjects.

The sensitivity and specificity of FLYRCADO PET MPI for the detection of significant CAD, defined as the presence of significant stenosis in at least one major epicardial coronary artery or major branch by QCA or as history of myocardial infarction are reported in Table 7. Results for both ≥50% stenosis and a secondary analysis using a threshold of ≥70% stenosis for significant CAD are shown.

Table 7. Diagnostic Performance of FLYRCADO PET MPI in Study 2 (N = 755)
 | ≥50% Stenosis or Confirmed MI Reference Standard |  | ≥70% Stenosis or Confirmed MI Reference Standard
Reader | Sensitivity (95% CI) N=352 | Specificity (95% CI) N=403 | Sensitivity (95% CI) N=245 | Specificity (95% CI) N=510
Reader 1 | 73% (68%, 78%) | 73% (68%, 77%) | 82% (77%, 87%) | 68% (63%, 71%)
Reader 2 | 63% (57%, 67%) | 86% (82%, 89%) | 72% (66%, 78%) | 80% (77%, 83%)
Reader 3 | 77% (72%, 80%) | 66% (62%, 71%) | 85% (80%, 89%) | 61% (57%, 66%)
Abbreviations: CI = confidence interval, MI = myocardial infarction, MPI = myocardial perfusion imaging

From a blinded re-evaluation of a randomly selected 10% of PET MPI images presented during the main reading sessions, intra-reader agreement ranged from 90% to 95% for the three readers.

Using a 50% stenosis threshold, sensitivity of SPECT MPI was 43% to 58% for the three readers, with the lower bound of the 95% confidence intervals ranging from 38% to 53%, and specificity for SPECT MPI was 80% to 92%, with the lower bound of the 95% confidence intervals ranging from 76% to 89%.

16 HOW SUPPLIED/STORAGE AND HANDLING

How Supplied

FLYRCADO (flurpiridaz F 18) injection is a clear, colorless to yellow solution containing 190 MBq/mL to 2,050 MBq/mL (5 mCi/mL to 55 mCi/mL) of flurpiridaz F 18 at end of synthesis, supplied in a shielded multiple-dose vial (NDC 0407-8787-01) with up to 30 mL fill volume.

Storage and Handling

Store FLYRCADO at 2°C to 30°C (36°F to 86°F); excursions to -20°C (-4°F) (up to 2 hours) or to 50°C (122°F) (up to 8 hours) may be permitted. Store FLYRCADO within radiation shielding. The product does not contain a preservative.

Do not use and discard FLYRCADO 8 hours after end of synthesis or when the activity falls below the radioactivity requirement at the time of injection, whichever is earlier. The expiration date and time are provided on the shield label.

Dispose of the product in accordance with all federal, state, and local laws and institutional requirements.

This preparation is for use by persons licensed by the Nuclear Regulatory Commission or the relevant regulatory authority of an Agreement State.

17 PATIENT COUNSELING INFORMATION

Adequate Hydration

Instruct patients to drink water to ensure adequate hydration prior to administration of FLYRCADO and to continue drinking and voiding frequently during the first hours following administration to reduce radiation exposure [see Warnings and Precautions (5.2)].

Pregnancy

Inform pregnant women of the risks of fetal exposure to radiation dose if they undergo a radionuclide procedure and the potential risk of exposure to ethanol which is present in FLYRCADO [see Use in Specific Populations (8.1)].

Lactation

Advise a lactating woman to temporarily discontinue breastfeeding and to pump and discard breast milk for at least 8 hours after FLYRCADO administration to minimize radiation exposure to a breastfed infant [see Use in Specific Populations (8.2)].

Distributed by
GE Healthcare Inc.
Arlington Heights, IL 60004
USA

FLYRCADO™ is a trademark of GE HealthCare.

GE is a trademark of General Electric Company used under trademark license.

© 2025 GE HealthCare

PRINCIPAL DISPLAY PANEL - 30 mL Vial Label

NDC 0407-8787-01
Multiple-Dose Vial
Non-Pyrogenic
Sterile

Flyrcado™
(flurpiridaz F 18) injection
190 MBq/mL to 2,050 MBq/mL
(5 mCi/mL to 55 mCi/mL) at end of synthesis
Diagnostic - For Intravenous Use Only

CAUTION
RADIOACTIVE
MATERIAL

Total: ______MBq (____mCi) in_____mL at _____:_____ on date ___________

Concentration: ____MBq/mL (____mCi/mL) Exp Date_________ Exp Time__________

Batch No.: _______________ Date: ________________ Vial No.: __________

Store FLYRCADO at 2°C to 30°C (36°F to 86°F); excursions to -20°C (-4°F) (up to 2 hours) or to 50°C
(122°F) (up to 8 hours) may be permitted.
Recommended Dosage: See Prescribing Information

Distributed by GE Healthcare Inc., Arlington Heights, IL 60004, U.S.A.

Rx ONLY

200112-0B

PRINCIPAL DISPLAY PANEL - 30 mL Shield Label

NDC 0407-8787-01
Non-Pyrogenic
Sterile

Flyrcado™
(flurpiridaz F 18) injection

CAUTION
RADIOACTIVE
MATERIAL

Multiple-Dose Vial
190 MBq/mL to 2,050 MBq/mL
(5 mCi/mL to 55 mCi/mL) at end of synthesis
Diagnostic - For Intravenous Use Only

Total _____MBq (___mCi) in ____mL at____:____ on date________

Batch No.:_____________ Exp. Date:_______ Exp. Time:____:____

Concentration:_______MBq/mL (____mCi/mL) Vial No.: ____________

Each mL contains up to 2.3 micrograms flurpiridaz, 45 mg hydroxypropyl-
β-cyclodextrin, 35 mg L-(+)-ascorbic acid, 8.2 mg sodium hydroxide, and
55.2 mg anhydrous ethanol in water for injection.

Store Flyrcado at 2°C to 30°C (36°F to 86°F); excursions to -20°C (-4°F) (up
to 2 hours) or to 50°C (122°F) (up to 8 hours) may be permitted.

Recommended Dosage: See Prescribing Information

Distributed by GE Healthcare Inc., Arlington Heights, IL 60004, U.S.A.

Rx ONLY

200113-0B